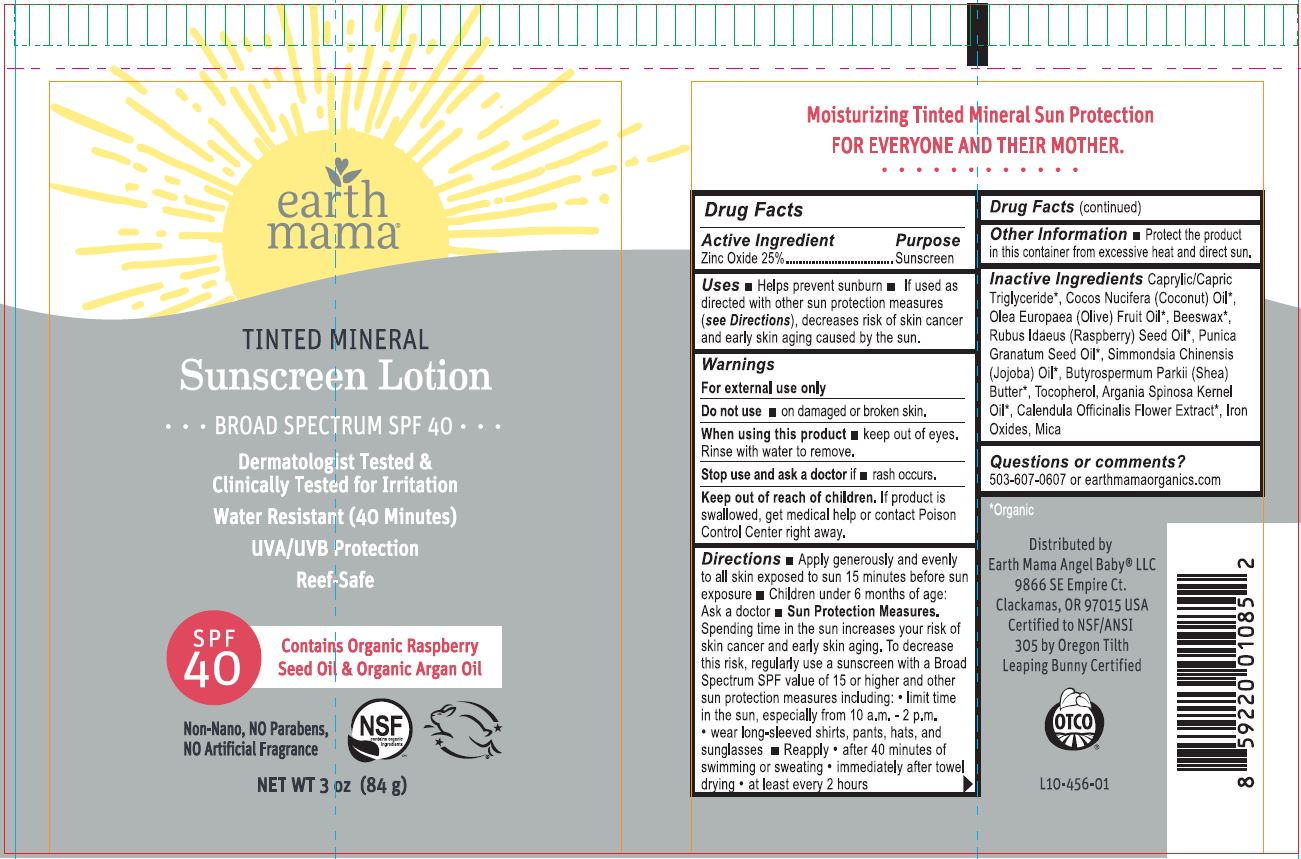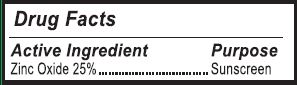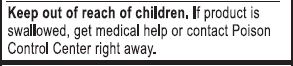 DRUG LABEL: Skin Protectant
NDC: 62932-227 | Form: LOTION
Manufacturer: Private Label Select Ltd CO
Category: otc | Type: HUMAN OTC DRUG LABEL
Date: 20220104

ACTIVE INGREDIENTS: ZINC OXIDE 25 g/100 g
INACTIVE INGREDIENTS: MEDIUM-CHAIN TRIGLYCERIDES; POMEGRANATE SEED OIL; .BETA.-TOCOPHEROL; .DELTA.-TOCOPHEROL; FERRIC OXIDE RED; CALENDULA OFFICINALIS FLOWER; OLIVE OIL; FERRIC OXYHYDROXIDE; .GAMMA.-TOCOPHEROL; FERROSOFERRIC OXIDE; ARGAN OIL; MICA; SHEA BUTTER; JOJOBA OIL; .ALPHA.-TOCOPHEROL, D-; COCONUT OIL; WHITE WAX; RASPBERRY SEED OIL

Earth Mama Tinted Mineral Sunscreen Lotion Broad Spectrum SPF 40